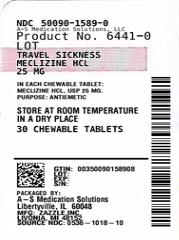 DRUG LABEL: Rugby Travel Sickness
NDC: 50090-1589 | Form: TABLET, CHEWABLE
Manufacturer: A-S Medication Solutions
Category: otc | Type: HUMAN OTC DRUG LABEL
Date: 20210223

ACTIVE INGREDIENTS: MECLIZINE HYDROCHLORIDE 25 mg/1 1
INACTIVE INGREDIENTS: ASPARTAME; CROSCARMELLOSE SODIUM; DEXTROSE, UNSPECIFIED FORM; FD&C RED NO. 40; MAGNESIUM STEARATE; MALTODEXTRIN; MICROCRYSTALLINE CELLULOSE; SILICON DIOXIDE; SODIUM SULFATE; SUCROSE; TRICALCIUM PHOSPHATE

TRAVEL SICKNESS CHEWABLE TABLETS

Drug Facts

Active ingredient (in each chewable tablet)

Meclizine HCl USP 25 mg

Purpose

Antiemetic

INDICATIONS AND USAGE

Uses prevents and treats nausea, vomiting or dizziness due to motion sickness

Warnings

Do not use in children under 12 years of age unless directed by a doctor

Ask a doctor before use if you have

- glaucoma
- a breathing problem such as emphysema or chronic bronchitis
- trouble urinating due to an enlarged prostate gland

Ask a doctor or pharmacist before use it you are taking sedatives or tranquilizers.

When using this product

- may cause drowsiness
- alcohol, sedatives, and tranquilizers may increase drowsiness
- avoid alcoholic drinks
- use caution when driving a motor vehicle or operating machinery

PREGNANCY OR BREAST FEEDING

If pregnant or breast-feeding, ask a health professional before use.

Keep out of reach of children. In case of overdose, get medical help or contact the poison control center immediately.

Directions

- Dosage should be taken one hour before travel starts
- Adults and children 12 years of age and older: Chew 1-2 tablets once daily, or as directed by a doctor
- Children under 12 years: do not give this product to children under 12 years of age unless directed by a doctor

Other information

- Phenylketonurics: Contains Phenylalanine 0.28 mg per tablet
- Store at room temperature in a dry place
- Keep lid tightly closed

Inactive ingredients

aspartame, croscarmellose sodium, dextrose, FD&C Red #40 Lake, magnesium stearate, maltodextrin, microcrystalline cellulose, natural and artificial flavors, silicon dioxide, sodium sulfate, sugar, tricalcium phosphate.

Questions or comments?

call 1-800-645-2158

OTHER SAFETY INFORMATION

TAMPER EVIDENT: DO NOT USE IF IMPRINTED SAFETY SEAL UNDER CAP IS BROKEN OR MISSING

Distributed by: Rugby Laboratories

17177 N. Laurel Park Drive, Suite 233, Livonia, MI 48152

HOW SUPPLIED

Product: 50090-1589

NDC: 50090-1589-0 30 TABLET, CHEWABLE in a BOTTLE